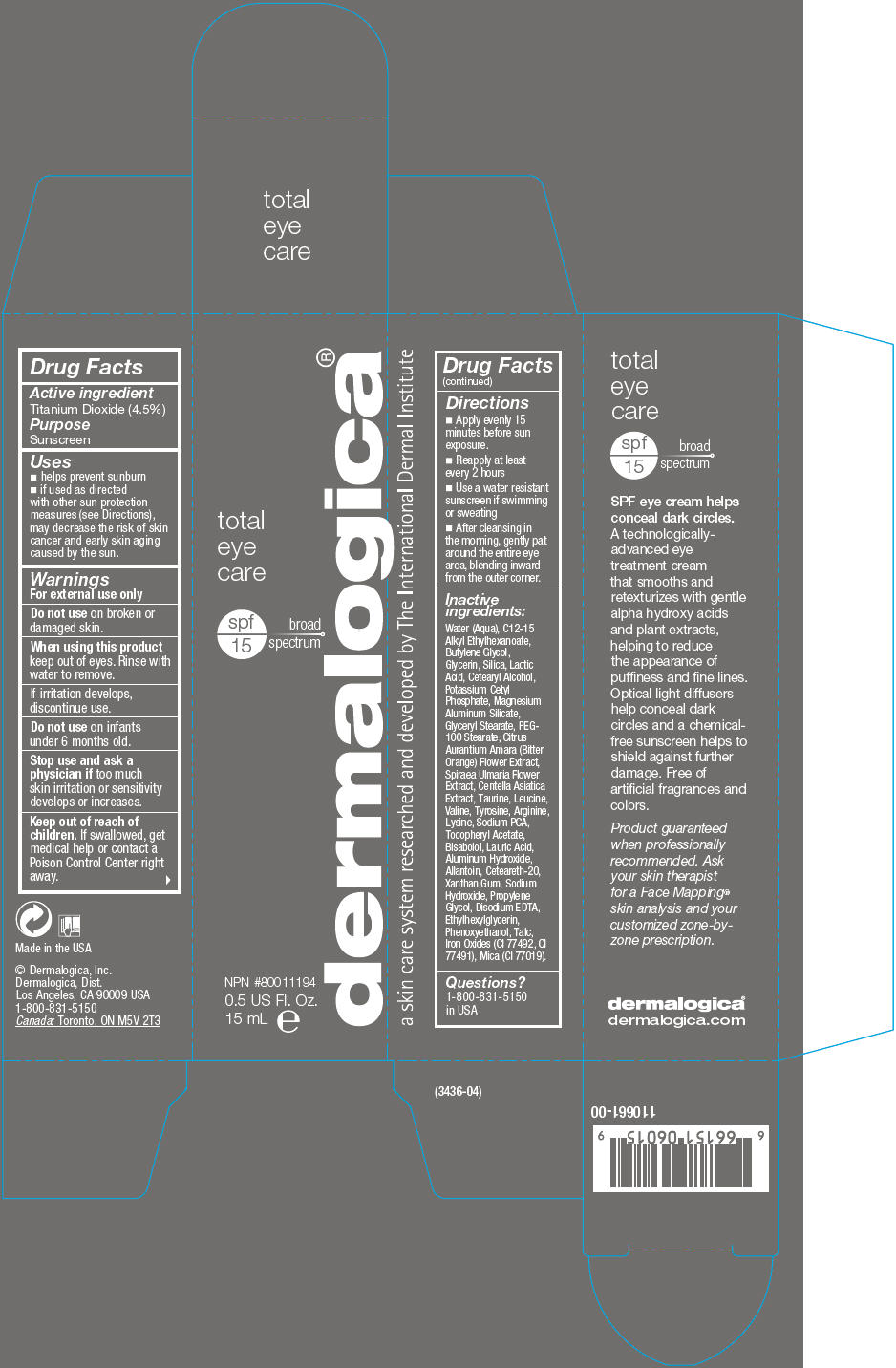 DRUG LABEL: Total Eye Care 
NDC: 68479-360 | Form: LOTION
Manufacturer: Dermalogica
Category: otc | Type: HUMAN OTC DRUG LABEL
Date: 20131223

ACTIVE INGREDIENTS: Titanium Dioxide 45 mg/1 mL
INACTIVE INGREDIENTS: Water; Butylene Glycol; Glycerin; Silicon Dioxide; Lactic Acid; Cetostearyl Alcohol; Potassium Cetyl Phosphate; Magnesium Aluminum Silicate; Glyceryl Monostearate; PEG-100 Stearate; Polyoxyl 20 Cetostearyl Ether; Citrus Aurantium Flower; Phenoxyethanol; Propylene Glycol; Sodium Pyrrolidone Carboxylate; Filipendula Ulmaria Flower; Centella Asiatica; Sodium Hydroxide; Aluminum Hydroxide; Lysine; Xanthan Gum; Levomenol; Arginine; Lauric Acid; Edetate Disodium; Taurine; Tyrosine; Ethylhexylglycerin; .Alpha.-Tocopherol Acetate; Allantoin; Leucine; Valine; Talc; FERRIC OXIDE YELLOW; BARIUM CARBONATE; FERRIC OXIDE RED

Total Eye Care
SPF 15

Drug Facts

Active ingredient

Titanium Dioxide (4.5%)

Purpose

Sunscreen

Uses

- helps prevent sunburn
- if used as directed with other sun protection measures (see Directions), may decrease the risk of skin cancer and early skin aging caused by the sun.

Warnings

For external use only

Do not use on broken or damaged skin.

When using this product keep out of eyes. Rinse with water to remove.

If irritation develops, discontinue use.

Do not use on infants under 6 months old.

Stop use and ask a physician if too much skin irritation or sensitivity develops or increases.

Keep out of reach of children. If swallowed, get medical help or contact a Poison Control Center right away.

Directions

- Apply evenly 15 minutes before sun exposure.
- Reapply at least every 2 hours
- Use a water resistant sunscreen if swimming or sweating
- After cleansing in the morning, gently pat around the entire eye area, blending inward from the outer corner.

Inactive ingredients

Water (Aqua), C12-15 Alkyl Ethylhexanoate, Butylene Glycol, Glycerin, Silica, Lactic Acid, Cetearyl Alcohol, Potassium Cetyl Phosphate, Magnesium Aluminum Silicate, Glyceryl Stearate, PEG-100 Stearate, Citrus Aurantium Amara (Bitter Orange) Flower Extract, Spiraea Ulmaria Flower Extract, Centella Asiatica Extract, Taurine, Leucine, Valine, Tyrosine, Arginine, Lysine, Sodium PCA, Tocopheryl Acetate, Bisabolol, Lauric Acid, Aluminum Hydroxide, Allantoin, Ceteareth-20, Xanthan Gum, Sodium Hydroxide, Propylene Glycol, Disodium EDTA, Ethylhexylglycerin, Phenoxyethanol, Talc, Iron Oxides (CI 77492, CI 77491), Mica (CI 77019).

Questions?

1-800-831-5150 in USA

PRINCIPAL DISPLAY PANEL - 15 mL Tube Carton

total
eye
care

spf
15
broad
spectrum

NPN #80011194
0.5 US Fl. Oz.
15 mL e

dermalogica®